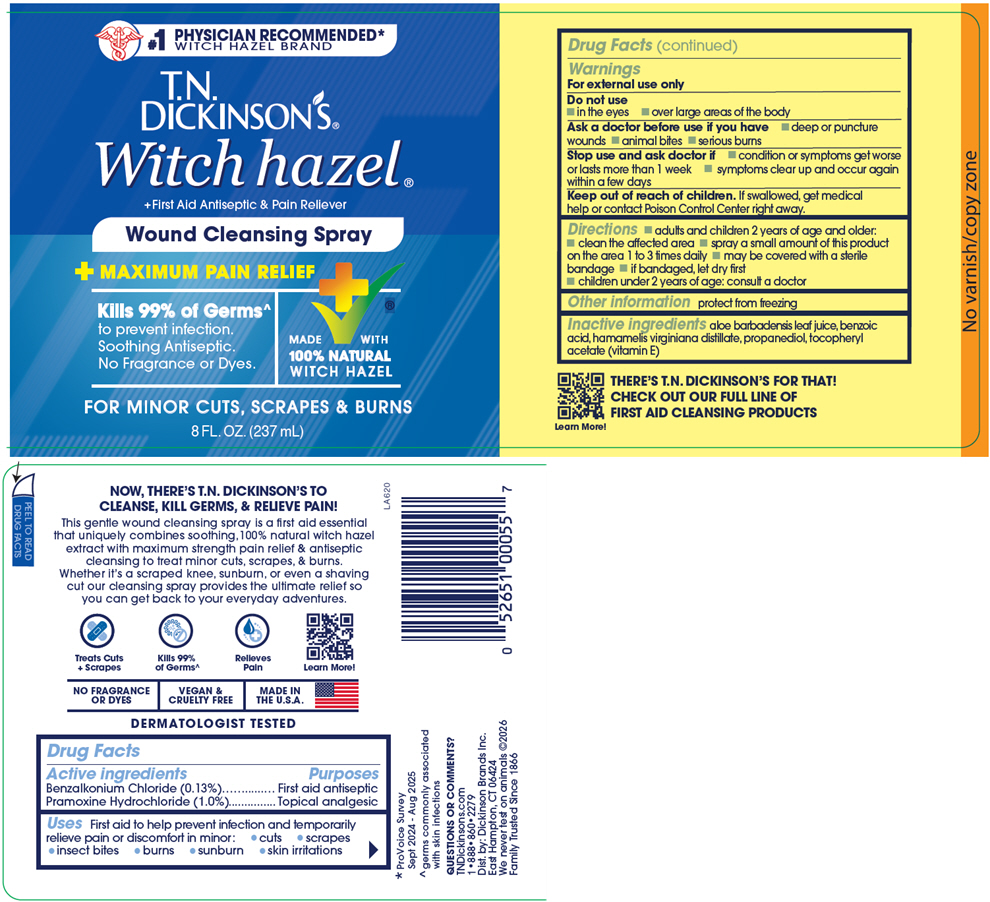 DRUG LABEL: T.N. Dickinsons Wound Cleansing
NDC: 52651-055 | Form: LIQUID
Manufacturer: Dickinson Brands Inc.
Category: otc | Type: HUMAN OTC DRUG LABEL
Date: 20251201

ACTIVE INGREDIENTS: BENZALKONIUM CHLORIDE 0.0013 g/1 mL; PRAMOXINE HYDROCHLORIDE 0.01 g/1 mL
INACTIVE INGREDIENTS: ALOE VERA LEAF JUICE; BENZOIC ACID; HAMAMELIS VIRGINIANA TOP WATER; PROPANEDIOL; .ALPHA.-TOCOPHEROL ACETATE

T.N. Dickinson's® Wound Cleansing

Drug Facts

ACTIVE INGREDIENT

PURPOSE

Active ingredients | Purposes
Benzalkonium Chloride (0.13%) | First aid antiseptic
Pramoxine Hydrochloride (1.0%) | Topical analgesic

Uses

First aid to help prevent infection and temporarily relieve pain or discomfort in minor:

- cuts
- scrapes
- insect bites
- burns
- sunburn
- skin irritations

Warnings

For external use only

Do not use

- in the eyes
- over large areas of the body

Ask a doctor before use if you have

- deep or puncture wounds
- animal bites
- serious burns

Stop use and ask doctor if

- condition or symptoms get worse or lasts more than 1 week
- symptoms clear up and occur again within a few days

Keep out of reach of children. If swallowed, get medical help or contact Poison Control Center right away.

Directions

- adults and children 2 years of age and older:
  - clean the affected area
  - spray a small amount of this product on the area 1 to 3 times daily
  - may be covered with a sterile bandage
  - if bandaged, let dry first
- children under 2 years of age: consult a doctor

Other information

protect from freezing

Inactive ingredients

aloe barbadensis leaf juice, benzoic acid, hamamelis virginiana distillate, propanediol, tocopheryl acetate (vitamin E)

QUESTIONS OR COMMENTS?

TNDickinsons.com
1•888•860•2279

Dist. by: Dickinson Brands Inc.
East Hampton, CT 06424

PRINCIPAL DISPLAY PANEL - 237 mL Bottle Label

#1 PHYSICIAN RECOMMENDED*
WITCH HAZEL BRAND

T.N.
DICKINSON'S®
Witch hazel®
+First Aid Antiseptic & Pain Reliever

Wound Cleansing Spray

+ MAXIMUM PAIN RELIEF

Kills 99% of Germs^
to prevent infection.
Soothing Antiseptic.
No Fragrance or Dyes.

MADE WITH
100% NATURAL
WITCH HAZEL

FOR MINOR CUTS, SCRAPES & BURNS

8 FL. OZ. (237 mL)